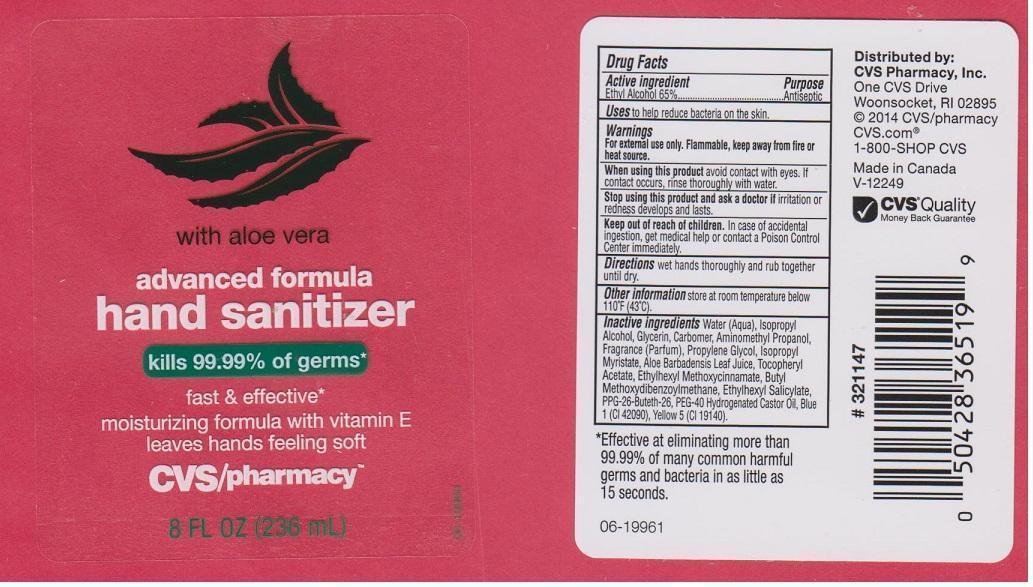 DRUG LABEL: CVS PHARMACY
NDC: 59779-744 | Form: LIQUID
Manufacturer: CVS PHARMACY
Category: otc | Type: HUMAN OTC DRUG LABEL
Date: 20141118

ACTIVE INGREDIENTS: ALCOHOL 650 mg/1 mL
INACTIVE INGREDIENTS: WATER; ISOPROPYL ALCOHOL; GLYCERIN; CARBOMER 934; AMINOMETHYLPROPANOL; PROPYLENE GLYCOL; ISOPROPYL MYRISTATE; ALOE VERA LEAF; .ALPHA.-TOCOPHEROL ACETATE; OCTINOXATE; AVOBENZONE; OCTISALATE; PPG-26-BUTETH-26; POLYOXYL 40 HYDROGENATED CASTOR OIL; FD&C BLUE NO. 1; FD&C YELLOW NO. 5

DRUG FACTS

ACTIVE INGREDIENT

ETHYL ALCOHOL 65%

PURPOSE

ANTISEPTIC

USES

TO HELP REDUCE BACTERIA ON THE SKIN

WARNINGS

FOR EXTERNAL USE ONLY. FLAMMABLE, KEEP AWAY FROM FIRE OR HEAT SOURCE

WHEN USING THIS PRODUCT

AVOID CONTACT WITH EYES. IF CONTACT OCCURS, RINSE THOROUGHLY WITH WATER

STOP USING THIS PRODUCT AND ASK A DOCTOR IF

IRRITATION OR REDNESS DEVELOPS AND LASTS

KEEP OUT OF REACH OF CHILDREN

IN CASE OF ACCIDENTAL INGESTION, GET MEDICAL HELP OR CONTACT A POISON CONTROL CENTER IMMEDIATELY

DIRECTIONS

WET HANDS THOROUGHLY AND RUB TOGETHER UNTIL DRY

OTHER INFORMATION

STORE AT ROOM TEMPERATURE BELOW 110°F (43°C)

INACTIVE INGREDIENTS

WATER (AQUA), ISOPROPYL ALCOHOL, GLYCERIN, CARBOMER, AMINOMETHYL PROPANOL, FRAGRANCE (PARFUM), PROPYLENE GLYCOL, ISOPROPYL MYRISTATE, ALOE BARBADENSIS LEAF JUICE, TOCOPHERYL ACETATE, ETHYLHEXYL METHOXYCINNAMATE, BUTYL METHYOXYDIBENZOYLMETHANE, ETHYLHEXYL SALICYLATE, PPG-26-BUTETH-26, PEG-40 HYDROGENATED CASTOR OIL, BLUE 1 (CI 42090), YELLOW 5 (CI 19140)